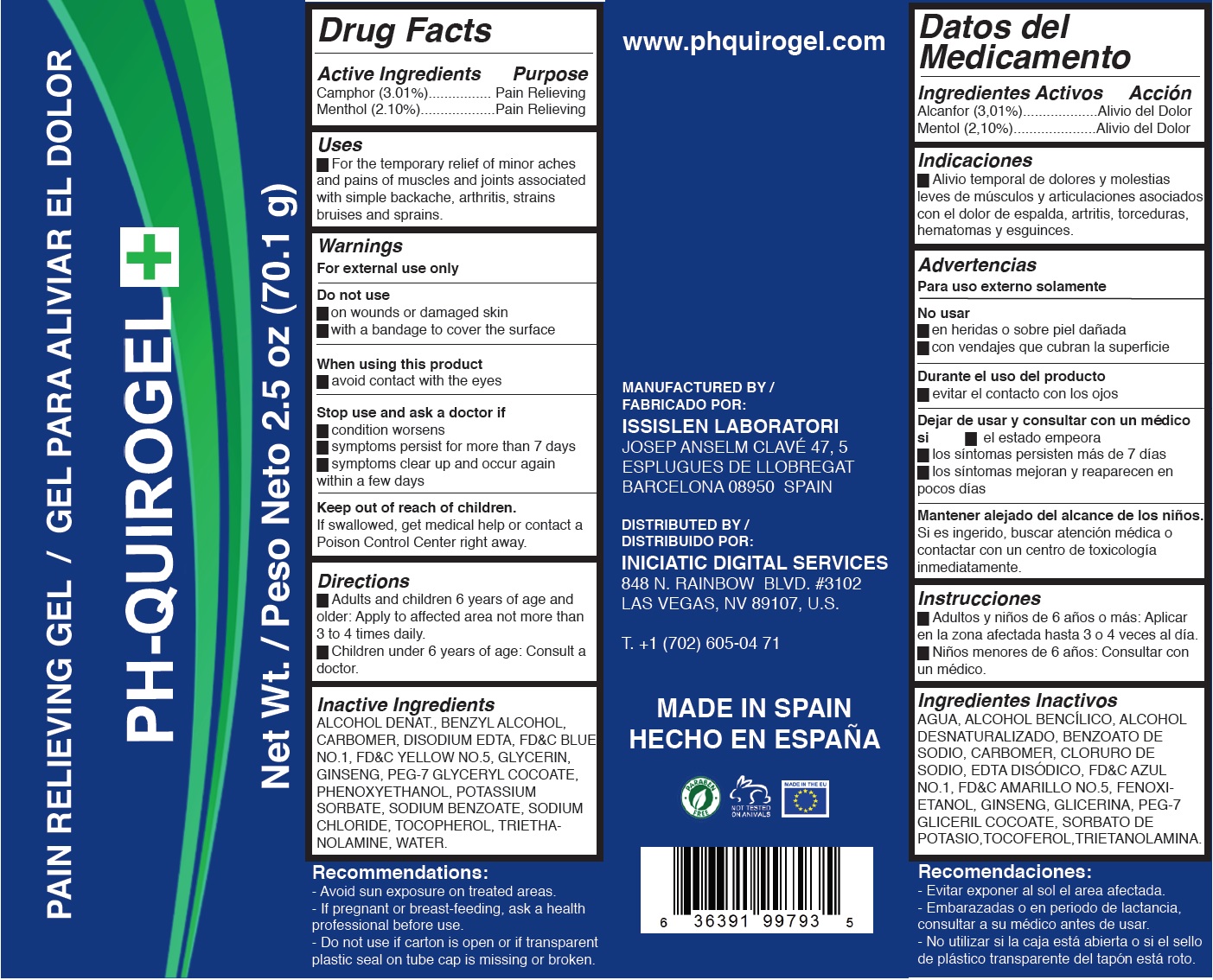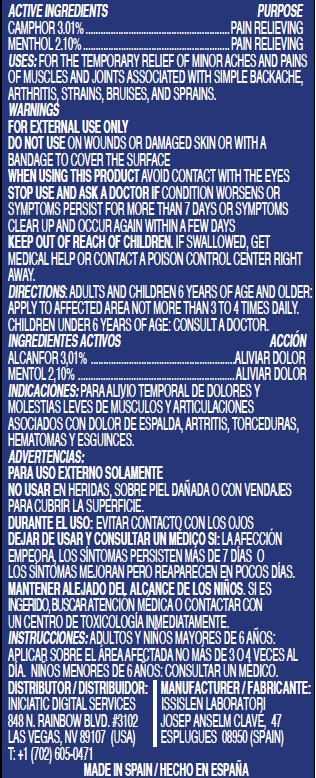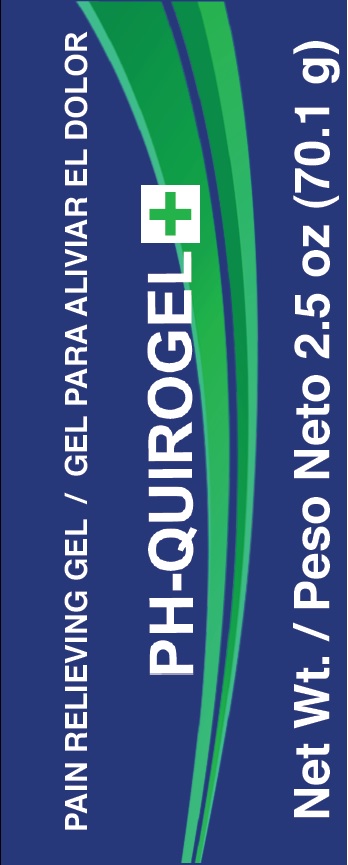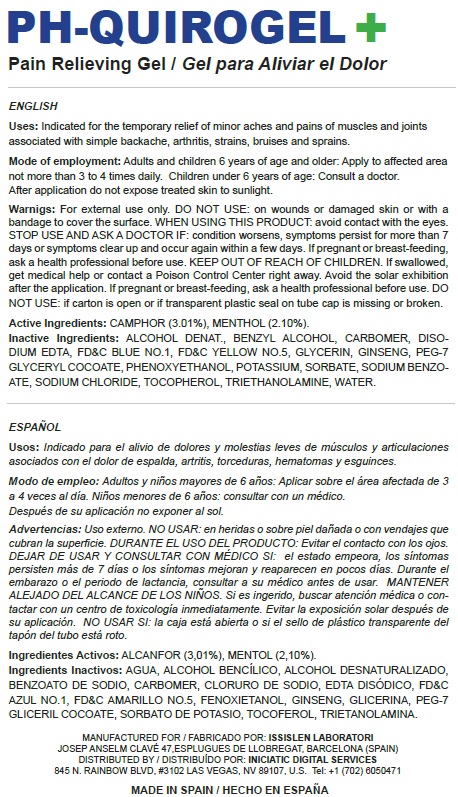 DRUG LABEL: PHQUIROGEL
NDC: 70544-001 | Form: GEL
Manufacturer: Issislen Laboratori S.L.
Category: otc | Type: HUMAN OTC DRUG LABEL
Date: 20160425

ACTIVE INGREDIENTS: CAMPHOR (SYNTHETIC) 30.1 mg/1 mL; MENTHOL 21 mg/1 mL
INACTIVE INGREDIENTS: ALCOHOL; BENZYL ALCOHOL; CARBOXYPOLYMETHYLENE; EDETATE DISODIUM; FD&C BLUE NO. 1; FD&C YELLOW NO. 5; GLYCERIN; ASIAN GINSENG; PEG-7 GLYCERYL COCOATE; PHENOXYETHANOL; POTASSIUM SORBATE; SODIUM BENZOATE; SODIUM CHLORIDE; TOCOPHEROL; TROLAMINE; WATER

PH-QUIROGEL+ Pain Relieving Gel

Active Ingredients

Camphor (3.01%)

Menthol (2.10%)

Purpose

Pain Relieving

Uses

- For the temporary relief of minor aches and pains of muscles and joints associated with simple backache, arthritis, strains bruises and sprains.

Warnings

For external use only

Do not use

- on wounds or damaged skin
- with a bandage to cover the surface

When using this product

- avoid contact with the eyes

Stop use and ask a doctor if

- condition worsens
- symptoms persist for more than 7 days
- symptoms clear up and occur again within a few days

Keep out of reach of children.

If swallowed, get medical help or contact a Poison Control Center right away.

Directions

- Adults and children 6 years of age and older: Apply to affected area not more than 3 to 4 times daily.
- Children under 6 years of age: Consult a doctor.

Inactive Ingredients

ALCOHOL DENAT., BENZYL ALCOHOL, CARBOMER, DISODIUM EDTA, FD&C BLUE NO.1, FD&C YELLOW NO.5, GLYCERIN, GINSENG, PEG-7 GLYCERYL COCOATE, PHENOXYETHANOL, POTASSIUM SORBATE, SODIUM BENZOATE, SODIUM CHLORIDE, TOCOPHEROL, TRIETHANOLAMINE,
WATER.